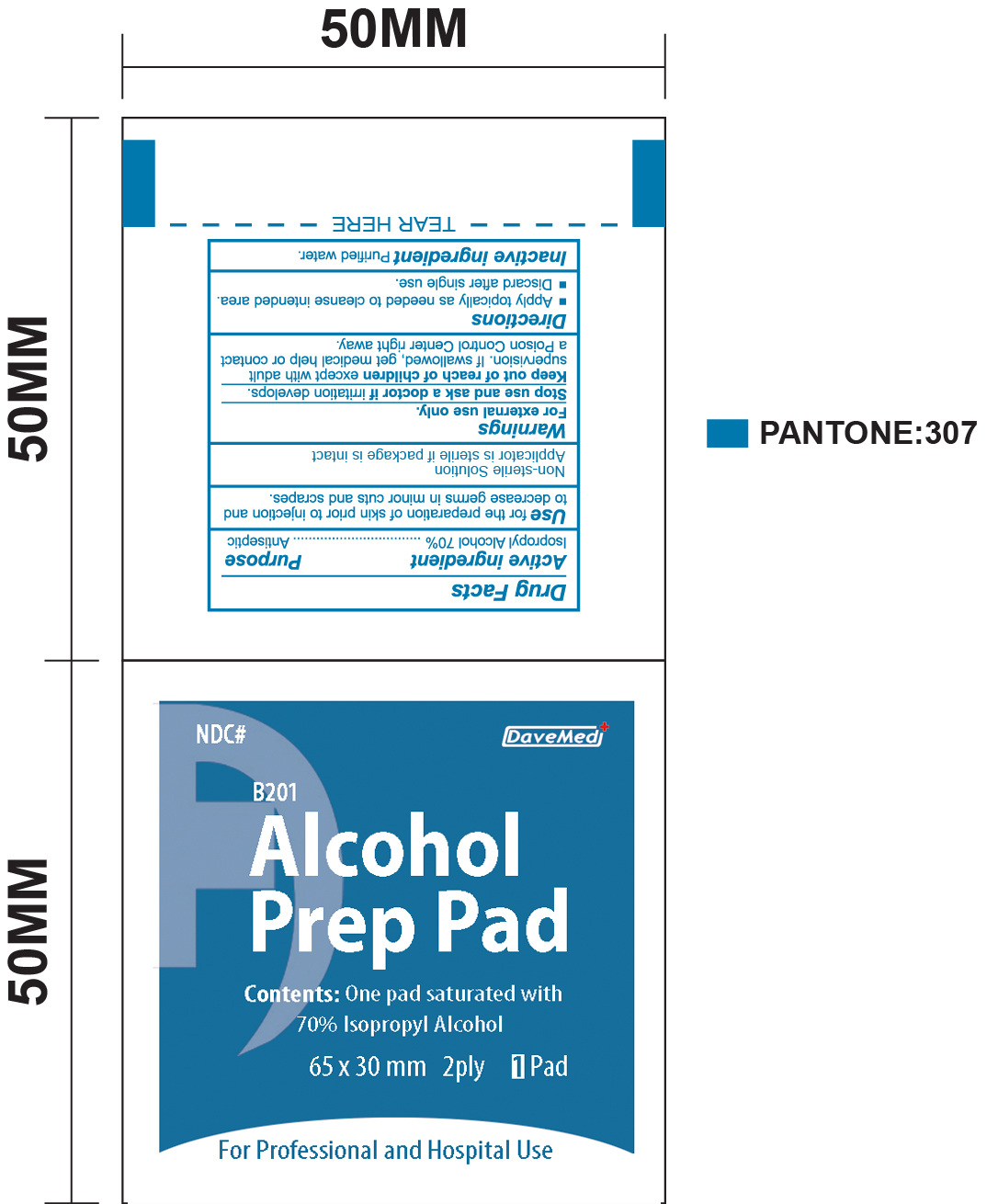 DRUG LABEL: Alcohol Prep Pad
NDC: 70897-007 | Form: SWAB
Manufacturer: Davemed Healthcare Co., Ltd
Category: otc | Type: HUMAN OTC DRUG LABEL
Date: 20190124

ACTIVE INGREDIENTS: ISOPROPYL ALCOHOL 0.7 mL/1 1
INACTIVE INGREDIENTS: WATER

ALCOHOL PREP PAD

ACTIVE INGREDIENT

Isopropyl Alcohol 70%

PURPOSE

Antiseptic

Keep out of reach of children except with adult supervision. If swallowed, get medical help or contact a Poison Control Center right away.

USE

For preparation of the skin prior to an injection and to decrease germs in minor cuts and scrapes.

WARNINGS

For external use only.

Stop and ask a doctor if irritation develops

DIRECTIONS

- Apply topically as needed to cleanse intended area.
- Discard after single use

INACTIVE INGREDIENT

Purified Water